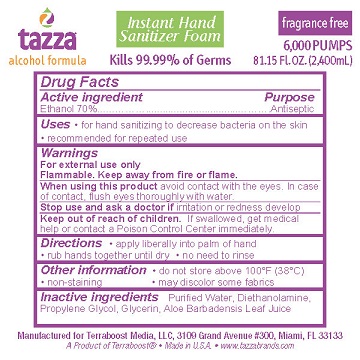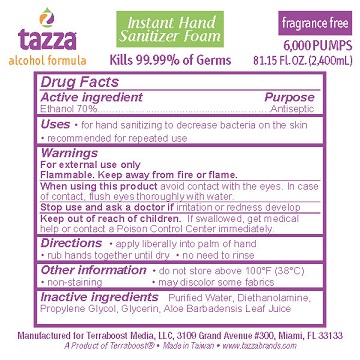 DRUG LABEL: Hand Sanitizer
NDC: 76370-0005 | Form: LIQUID
Manufacturer: Tazza Brands East Inc.
Category: otc | Type: HUMAN OTC DRUG LABEL
Date: 20240124

ACTIVE INGREDIENTS: ALCOHOL 70 mL/100 mL
INACTIVE INGREDIENTS: DIETHANOLAMINE; WATER; ALOE VERA LEAF; GLYCERIN; PROPYLENE GLYCOL

TAZZA INSTANT HAND SANITIZER FOAM

Drug Facts

Active ingredient

Ethanol 70%

Purpose

Antiseptic

Uses

- for hand sanitizing to decrease bacteria on the skin
- recommended for repeated use

Warnings

For external use only

Flammable. Keep away from fire or flame.

When using this product avoid contact with eyes. In case of eye contact, flush eyes with water and seek medical help.

Stop use and ask a doctor if irritation or redness develop.

Keep out of reach of children. If swallowed, get medical help or contact a Poison Control Center immediately.

Directions

- apply liberally into palm of hand
- rub hands together until dry
- no need to rinse

Other information

- do not store above 100°F (38°C)
- non-staining
- may discolor some fabrics

Inactive ingredients

Purified Water, Diethanolamine, Propylene Glycol, Glycerin, Aloe Barbadensis Leaf Juice.

Manufactured for Terraboost Media, LLC, 3109 Grand Avenue #300, Miami, FL 33133

A Product of Terraboost®

Made in Taiwan [Made in U.S.A.]

www.tazzabrands.com

PACKAGE LABEL

Tazza Instant Hand Sanitizer Foam

alcohol formula

Kills 99.99% of Germs

fragrance free

6,000 PUMPS

81.15 Fl.OZ. (2,400mL)